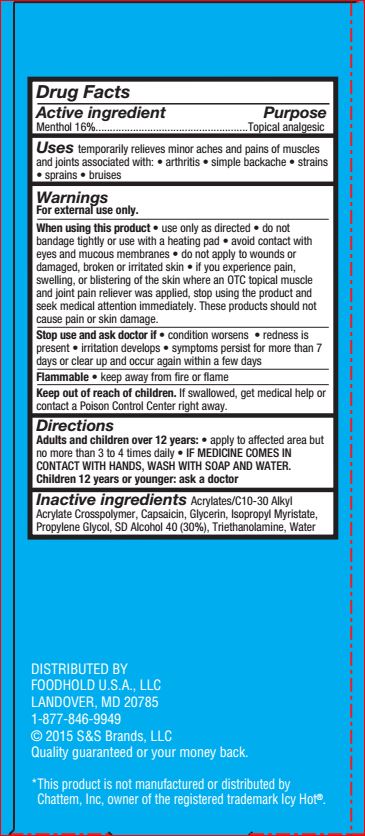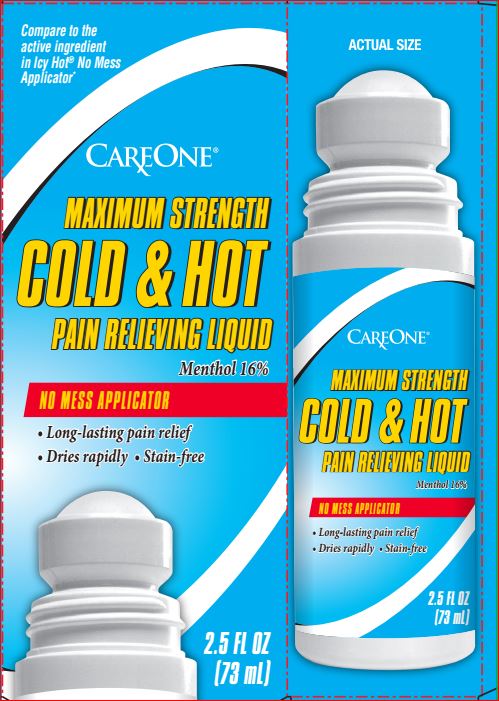 DRUG LABEL: Cold and Hot paim relieving
NDC: 41520-777 | Form: LIQUID
Manufacturer: CareOne
Category: otc | Type: HUMAN OTC DRUG LABEL
Date: 20180109

ACTIVE INGREDIENTS: MENTHOL 16 g/100 mL
INACTIVE INGREDIENTS: CARBOMER INTERPOLYMER TYPE A (ALLYL SUCROSE CROSSLINKED); Capsaicin; Glycerin; Isopropyl Myristate; Propylene Glycol; ALCOHOL; TROLAMINE; Water

Drug Facts

Active ingredient Purpose

Menthol 16%.....................................................Topical analgesic

Uses

temporarily relieves minor aches and pains of muscles
and joints associated with: • arthritis • simple backache • strains
• sprains • bruises

WARNINGS

For external use only.
When using this product • use only as directed • do not
bandage tightly or use with a heating pad • avoid contact with
eyes and mucous membranes • do not apply to wounds or
damaged, broken or irritated skin • if you experience pain,
swelling, or blistering of the skin where an OTC topical muscle
and joint pain reliever was applied, stop using the product and
seek medical attention immediately. These products should not
cause pain or skin damage.
Stop use and ask doctor if • condition worsens • redness is
present • irritation develops • symptoms persist for more than 7
days or clear up and occur again within a few days
Flammable • keep away from fire or flame

Keep out of reach of children.

If swallowed, get medical help or
contact a Poison Control Center right away.

Directions

Adults and children over 12 years: • apply to affected area but
no more than 3 to 4 times daily • IF MEDICINE COMES IN
CONTACT WITH HANDS, WASH WITH SOAP AND WATER.
Children 12 years or younger: ask a doctor

Inactive ingredients

Acrylates/C10-30 Alkyl
Acrylate Crosspolymer, Capsaicin, Glycerin, Isopropyl Myristate,
Propylene Glycol, SD Alcohol 40 (30%), Triethanolamine, Water